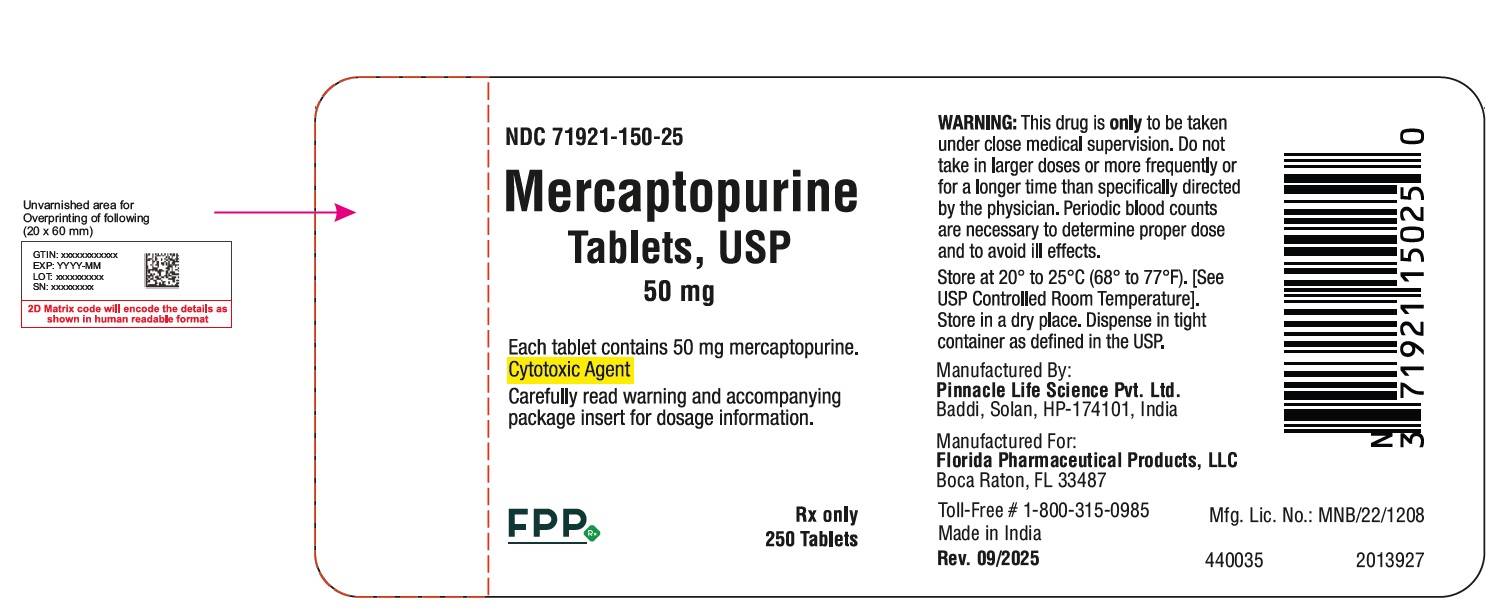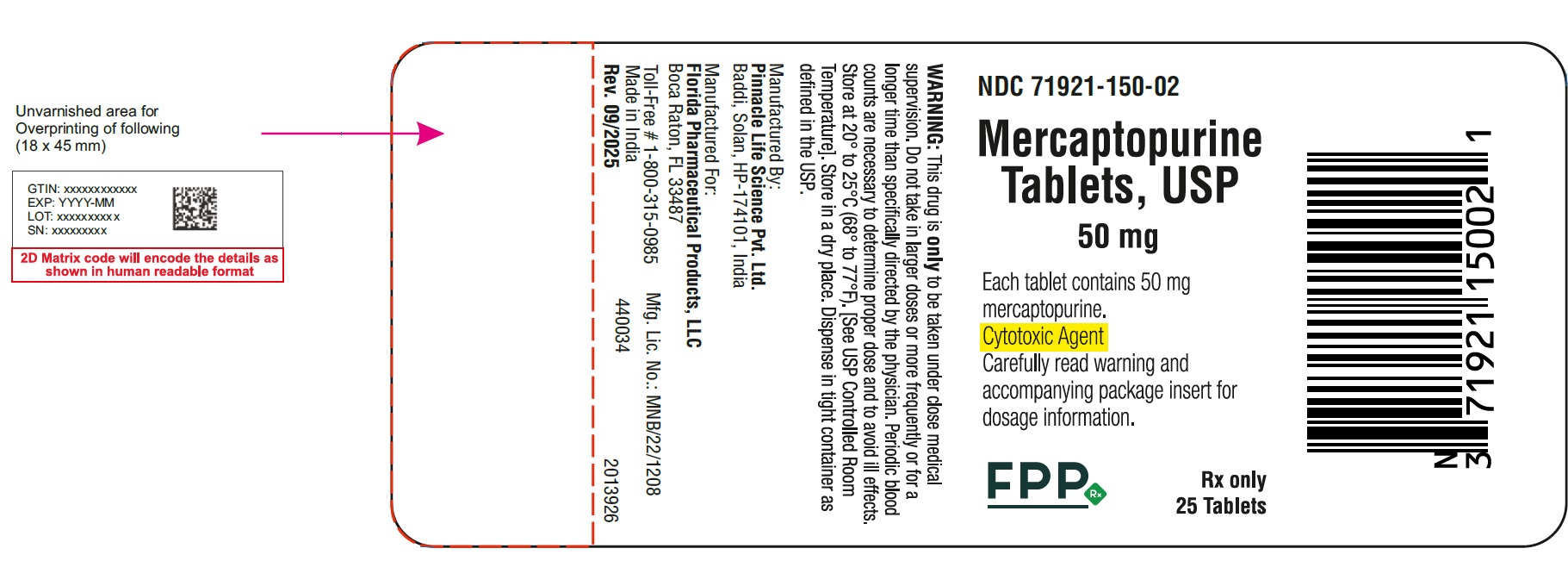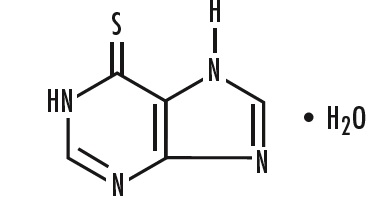 DRUG LABEL: Mercaptopurine
NDC: 71921-150 | Form: TABLET
Manufacturer: Florida Pharmaceutical Products, LLC
Category: prescription | Type: Human Prescription Drug Label
Date: 20260130

ACTIVE INGREDIENTS: MERCAPTOPURINE 50 mg/1 1
INACTIVE INGREDIENTS: LACTOSE MONOHYDRATE; STARCH, POTATO; STARCH, CORN; STEARIC ACID; MAGNESIUM STEARATE; WATER

HIGHLIGHTS OF PRESCRIBING INFORMATION

These highlights do not include all the information needed to use MERCAPTOPURINE TABLETS safely and effectively. See full prescribing information for MERCAPTOPURINE TABLETS.
MERCAPTOPURINE tablets, for oral use
Initial U.S. Approval:1953

RECENT MAJOR CHANGES

Warnings and Precautions, Hepatotoxicity (5.2) 07/2024

1 INDICATIONS & USAGE

Mercaptopurine tablets is a nucleoside metabolic inhibitor indicated for treatment of adult and pediatric patients with acute lymphoblastic leukemia (ALL) as part of a combination chemotherapy maintenance regimen. (1.1)

2 DOSAGE & ADMINISTRATION

- The recommended starting dose of mercaptopurine tablets is 1.5 mg/kg to 2.5 mg/kg orally once daily as part of a combination chemotherapy maintenance regimen. Adjust dose to maintain desirable absolute neutrophil count and for excessive myelosuppression. (2.1)
- Renal Impairment: Use the lowest recommended starting dose or increase the dosing interval. (2.3, 8.6)
- Hepatic Impairment: Use the lowest recommended starting dose. (2.3, 8.7)

3 DOSAGE FORMS & STRENGTHS

Tablets: 50 mg (3)

4 CONTRAINDICATIONS

None.

5 WARNINGS AND PRECAUTIONS

- Myelosuppression: Monitor complete blood count (CBC) and adjust the dose of mercaptopurine tablets for excessive myelosuppression. Consider testing in patients with severe myelosuppression or repeated episodes of myelosuppression for thiopurine S -methyltransferase (TPMT) or nucleotide diphosphatase (NUDT15) deficiency. Patients with homozygous or homozygous TPMT or NUDT15 deficiency may require a dose reduction. (2.2, 5.1)
- Hepatotoxicity: Monitor transaminases, alkaline phosphatase and bilirubin. Withhold mercaptopurine tablets at onset of hepatotoxicity. (5.2)
- Immunosuppression: Response to all vaccines may be diminished and there is a risk of infection with live virus vaccines. Consult immunization guidelines for immunocompromised patients. (5.3)
- Treatment Related Malignancies: Aggressive and fatal cases of hepatosplenic T-cell lymphoma have occurred. (5.4)
- Macrophage Activation Syndrome: Monitor for and treat promptly; discontinue mercaptopurine tablets. (5.5)
- Embryo-Fetal Toxicity: Can cause fetal harm. Advise patients of reproductive potential of the potential risk to a fetus and to use effective contraception. (5.6, 8.1, 8.3)

6 ADVERSE REACTIONS

The most common adverse reaction (>20%) is myelosuppression, including anemia, leukopenia and thrombocytopenia. Adverse reactions occurring in 5% to 20% of patients include anorexia, nausea, vomiting, diarrhea, malaise and rash. (6.1)

To report SUSPECTED ADVERSE REACTIONS, contact Florida Pharmaceutical Products, LLC at 1-800-315-0985 or FDA at 1-800-FDA-1088 or www.fda.gov/medwatch

7 DRUG INTERACTIONS

- Allopurinol: Reduce the dose of mercaptopurine tablets when co-administered with allopurinol. (2.4, 7.1)
- Warfarin: Mercaptopurine tablets may decrease the anticoagulant effect. (7.2)

8 USE IN SPECIFIC POPULATIONS

- Lactation: Advise not to breastfeed. (8.2)
- Infertility: Can impair fertility. (8.3)

FULL PRESCRIBING INFORMATION

1 INDICATIONS & USAGE

1.1 Acute Lymphoblastic Leukemia

Mercaptopurine tablets are indicated for treatment of adult and pediatric patients with acute lymphoblastic leukemia (ALL) as part of a combination chemotherapy maintenance regimen.

2 DOSAGE & ADMINISTRATION

2.1 Recommended Dosage

The recommended starting dosage of mercaptopurine tablets is 1.5 mg/kg to 2.5 mg/kg orally once daily as part of combination chemotherapy maintenance regimen. A recommended dosage for patients less than 17 kg is not achievable, because the only available strength is 50 mg. Take mercaptopurine tablets either consistently with or without food.

After initiating mercaptopurine tablets, monitor complete blood count (CBC) and adjust the dose to maintain absolute neutrophil count (ANC) at a desirable level and for excessive myelosuppression. Evaluate the bone marrow in patients with prolonged myelosuppression or repeated episodes of myelosuppression to assess leukemia status and marrow cellularity.

Evaluate thiopurine S-methyltransferase (TPMT) and nucleotide diphosphatase (NUDT15) status in patients with severe myelosuppression or repeated episodes or myelosuppression [see Dosage and Administration (2.2)].

Do not administer to patients who are unable to swallow tablets.

If a patient misses a dose, instruct the patient to continue with the next scheduled dose.

Mercaptopurine tablets is a cytotoxic drug. Follow special handling and disposal procedures.

2.2 Dosage Modifications in Patients with TPMT and NUDT15 Deficiency

Consider testing for TPMT and NUDT15 deficiency in patients who experience severe myelosuppression or repeated episodes of myelosuppression [see Warnings and Precautions (5.1), Clinical Pharmacology (12.5)].
Homozygous Deficiency in either TPMT or NUDT15
Patients with homozygous deficiency of either enzyme typically require 10% or less of the recommended dosage. Reduce the recommended starting dosage of mercaptopurine tablets in patients who are known to have homozygous TPMT or NUDT15 deficiency.
Heterozygous Deficiency in TPMT and/or NUDT15
Reduce the mercaptopurine tablets dose based on tolerability. Most patients with heterozygous TPMT or NUDT15 deficiency tolerate the recommended dosage, but some require a dose reduction based on adverse reactions. Patients who are heterozygous for both TPMT and NUDT15 may require more substantial dose reductions.

2.3 Dosage Modifications in Renal and Hepatic Impairment

Renal Impairment
Use the lowest recommended starting dosage for mercaptopurine tablets in patients with renal impairment (CLcr less than 50 mL/min). Adjust the dosage to maintain absolute neutrophil count (ANC) at a desirable level and for adverse reactions [see Uses in Specific Populations (8.6)].
Hepatic Impairment
Use the lowest recommended starting dosage for mercaptopurine tablets in patients with hepatic impairment. Adjust the dosage to maintain absolute neutrophil count (ANC) at a desirable level and for adverse reactions [see Uses in Specific Populations (8.7)].

2.4 Dosage Modification with Concomitant Use of Allopurinol

Reduce the dose of mercaptopurine tablets to one-third to one-quarter of the current dosage when coadministered with allopurinol [see Drug Interactions (7.1)].

3 DOSAGE FORMS & STRENGTHS

Tablets: 50 mg mercaptopurine, biconvex, round, pale yellow to buff, scored tablets imprinted with “9|3”

4 CONTRAINDICATIONS

None.

5 WARNINGS AND PRECAUTIONS

5.1 Myelosuppression

The most consistent, dose-related adverse reaction is myelosuppression, manifested by anemia, leukopenia, thrombocytopenia, or any combination of these. Monitor CBC and adjust the dosage of mercaptopurine tablets for excessive myelosuppression [see Dosage and Administration (2.1)].
Consider testing for TPMT or NUDT15 deficiency in patients with severe myelosuppression or repeated episodes of myelosuppression. TPMT genotyping or phenotyping (red blood cell TPMT activity) and NUDT15 genotyping can identify patients who have reduced activity of these enzymes. Patients with heterozygous or homozygous TPMT or NUDT15 deficiency may require a dose reduction [see Dosage and Administration (2.2), Clinical Pharmacology (12.5)].

Myelosuppression can be exacerbated by coadministration with allopurinol, aminosalicylates or other products that cause myelosuppression [see Drug Interactions (7.1, 7.3, 7.4)]. Reduce the dose of mercaptopurine tablets when coadministered with allopurinol [see Dosage and Administration (2.4)].

5.2 Hepatoxicity

Mercaptopurine is hepatotoxic. There are reports of deaths attributed to hepatic necrosis associated with the administration of mercaptopurine. Hepatic injury can occur with any dosage but seems to occur with greater frequency when the recommended dosage is exceeded. In some patients, jaundice has cleared following withdrawal of mercaptopurine and reappeared with rechallenge.

Usually, clinically detectable jaundice appears early in the course of treatment (1 to 2 months); however, jaundice has been reported as early as 1 week and as late as 8 years after the starting mercaptopurine. The hepatotoxicity has been associated in some cases with anorexia, diarrhea, jaundice, ascites, and pruritus. Hepatic encephalopathy has occurred.

Monitor serum transaminase levels, alkaline phosphatase, and bilirubin levels at weekly intervals when first beginning therapy and at monthly intervals thereafter. Monitor liver tests more frequently in patients who are receiving mercaptopurine tablets with other hepatotoxic products [see Drug Interactions (7.5)] or with known pre-existing liver disease. Withhold mercaptopurine tablets at onset of hepatotoxicity.

Intrahepatic Cholestasis of Pregnancy

Postmarketing cases of intrahepatic cholestasis of pregnancy (ICP) have been reported in patients with inflammatory bowel disease who received mercaptopurine during pregnancy. Mercaptopurine is not indicated for use in inflammatory bowel disease [see Indications and Usage (1.1)].

Discontinue Mercaptopurine if ICP develops in a pregnant woman.

5.3 Immunosuppression

Mercaptopurine is immunosuppressive and may impair the immune response to infectious agents or vaccines. Due to the immunosuppression associated with maintenance chemotherapy for ALL, response to all vaccines may be diminished and there is a risk of infection with live virus vaccines. Consult immunization guidelines for immunocompromised patients.

5.4 Treatment Related Malignancies

Hepatosplenic T-cell lymphoma has been reported in patients treated with mercaptopurine for inflammatory bowel disease (IBD), an unapproved use. Mercaptopurine is mutagenic in animals and humans, carcinogenic in animals, and may increase the risk of secondary malignancies.
Patients receiving immunosuppressive therapy, including mercaptopurine, are at an increased risk of developing lymphoproliferative disorders and other malignancies, notably skin cancers (melanoma and non-melanoma), sarcomas (Kaposi's and non-Kaposi's) and uterine cervical cancer in situ. The increased risk appears to be related to the degree and duration of immunosuppression. It has been reported that discontinuation of immunosuppression may provide partial regression of the lymphoproliferative disorder.
A treatment regimen containing multiple immunosuppressants (including thiopurines) should therefore be used with caution as this could lead to lymphoproliferative disorders, some with reported fatalities. A combination of multiple immunosuppressants, given concomitantly increases the risk of Epstein-Barr virus (EBV)-associated lymphoproliferative disorders.

5.5 Macrophage Activation Syndrome

Macrophage activation syndrome (MAS) (hemophagocytic lymphohistiocytosis) is a known, life-threatening disorder that may develop in patients with autoimmune conditions, in particular with inflammatory bowel disease (IBD), and there could potentially be an increased susceptibility for developing the condition with the use of mercaptopurine (an unapproved use). If MAS occurs, or is suspected, discontinue mercaptopurine tablets. Monitor for and promptly treat infections such as EBV and cytomegalovirus (CMV), as these are known triggers for MAS.

5.6 Embryo-Fetal Toxicity

Mercaptopurine tablets can cause fetal harm when administered to a pregnant woman. An increased incidence of miscarriage has been reported in women who received mercaptopurine in the first trimester of pregnancy. Adverse embryo-fetal findings, including miscarriage and stillbirth, have been reported in women who received mercaptopurine after the first trimester of pregnancy. Advise pregnant women of the potential risk to a fetus. Advise females of reproductive potential to use effective contraception during treatment with mercaptopurine tablets and for 6 months after the last dose. Advise males with female partners of reproductive potential to use effective contraception during treatment with mercaptopurine tablets and for 3 months after the last dose [see Use in Specific Populations (8.1, 8.3)].

6 ADVERSE REACTIONS

The following clinically significant adverse reactions are described elsewhere in the labeling:

- Myelosuppression [see Warnings and Precautions (5.1)]
- Hepatotoxicity [see Warnings and Precautions (5.2)]
- Immunosuppression [see Warnings and Precautions (5.3)]
- Treatment related malignancies [see Warnings and Precautions (5.4)]
- Macrophage activation syndrome [see Warnings and Precautions (5.5)]

6.1 Clinical Trials Experience

Because clinical trials are conducted under widely varying conditions, adverse reaction rates observed in the clinical trials of a drug cannot be directly compared to rates in the clinical trials of another drug and may not reflect the rates observed in practice.
Based on multicenter cooperative group ALL trials, the most common adverse reaction occurring in > 20% of patients was myelosuppression, including anemia, neutropenia, lymphopenia and thrombocytopenia. Adverse reactions occurring in 5% to 20% of patients included anorexia, nausea, vomiting, diarrhea, malaise and rash. Adverse reactions occurring in < 5 % of patients included urticaria, hyperuricemia, oral lesions, increased transaminases, hyperbilirubinemia, hyperpigmentation, infections, and pancreatitis. Oral lesions resemble thrush rather than antifolic ulcerations. Delayed or late adverse reactions include hepatic fibrosis, hyperbilirubinemia, alopecia, pulmonary fibrosis, oligospermia and secondary malignancies [see Warnings and Precautions (5.1, 5.2)].
Drug fever has been reported with mercaptopurine.
Additional adverse reactions that have been reported in patients who have received mercaptopurine include photosensitivity, hypoglycemia, and portal hypertension.

6.2 Postmarketing Experience

The following adverse reactions have been identified during postapproval use of mercaptopurine tablets. Because these reactions are reported voluntarily from a population of uncertain size, it is not always possible to reliably estimate their frequency or establish a causal relationship to drug exposure. These reactions include: intrahepatic cholestasis of pregnancy (ICP).

7 DRUG INTERACTIONS

7.1 Allopurinol

Allopurinol can inhibit the first-pass oxidative metabolism of mercaptopurine by xanthine oxidase, which can lead to an increased risk of mercaptopurine adverse reactions (i.e., myelosuppression, nausea, and vomiting) [see Warnings and Precautions (5.1), Adverse Reactions (6.1)]. Reduce the dose of mercaptopurine tablets when coadministered with allopurinol [see Dosage and Administration (2.4)].

7.2 Warfarin

The concomitant administration of mercaptopurine tablets and warfarin may decrease the anticoagulant effectiveness of warfarin. Monitor the international normalized ratio (INR) in patients receiving warfarin and adjust the warfarin dosage as appropriate.

7.3 Myelosuppresive Products

Mercaptopurine tablets can cause myelosuppression. Myelosuppression may be increased when mercaptopurine tablets is coadministered with other products that cause myelosuppression. Enhanced myelosuppression has been noted in some patients also receiving trimethoprim-sulfamethoxazole. Monitor the CBC and adjust the dose of mercaptopurine tablets for excessive myelosuppression [see Dosage and Administration (2.1), Warnings and Precautions (5.1)].

7.4 Aminosalicylates

Aminosalicylates (e.g., mesalamine, olsalazine or sulfasalazine) may inhibit the TPMT enzyme, which may increase the risk of myelosuppression when coadministered with mercaptopurine tablets. When aminosalicylates and mercaptopurine tablets are coadministered, use the lowest possible doses for each drug and monitor more frequently for myelosuppression [see Warnings and Precautions (5.1)].

7.5 Hepatotoxic Products

Mercaptopurine tablets can cause hepatotoxicity. Hepatotoxicity may be increased when mercaptopurine tablets is coadministered with other products that cause hepatotoxicity. Monitor liver tests more frequently in patients who are receiving mercaptopurine tablets with other hepatotoxic products [see Warnings and Precautions (5.2)].

8 USE IN SPECIFIC POPULATIONS

8.1 Pregnancy

Risk Summary
Mercaptopurine tablets can cause fetal harm when administered to a pregnant woman [see Clinical Pharmacology (12.1)]. Pregnant women who receive mercaptopurine have an increased incidence of miscarriage and stillbirth (see Data). Advise pregnant women of the potential risk to a fetus.
The estimated background risk of major birth defects and miscarriage for the indicated population(s) is unknown. All pregnancies have a background risk of birth defect, loss, or other adverse outcomes. In the U.S. general population, the estimated background risk of major birth defects and miscarriage in clinically recognized pregnancies is 2% to 4% and 15% to 20%, respectively.
Data
Human Data
Women receiving mercaptopurine in the first trimester of pregnancy have an increased incidence of miscarriage; the risk of malformation in offspring surviving first trimester exposure is not known. In a series of 28 women receiving mercaptopurine after the first trimester of pregnancy, 3 mothers died prior to delivery, 1 delivered a stillborn child, and 1 aborted; there were no cases of macroscopically abnormal fetuses.
Animal Data
Mercaptopurine was embryo-lethal and teratogenic in several animal species (rat, mouse, rabbit, and hamster) at doses less than the recommended human dose.

8.2 Lactation

Risk Summary
There are no data on the presence of mercaptopurine or its metabolites in human milk, the effects on the breastfed child, or the effects on milk production. Because of the potential for serious adverse reactions in the breastfed child, advise women not to breastfeed during treatment with mercaptopurine tablets and for 1 week after the last dose.

8.3 Females and Males of Reproductive Potential

Mercaptopurine tablets can cause fetal harm when administered to pregnant women [see Use in Specific Populations (8.1)].
Pregnancy Testing
Verify the pregnancy status in females of reproductive potential prior to initiating mercaptopurine tablets [see Use in Specific Populations (8.1)].
Contraception
Females
Advise females of reproductive potential to use effective contraception during treatment with mercaptopurine tablets and for 6 months after the last dose.
Males
Based on genotoxicity findings, advise males with female partners of reproductive potential to use effective contraception during treatment with mercaptopurine tablets and for 3 months after the last dose [see Nonclinical Toxicology (13.1)].

Infertility
Females and Males
Based on findings from animal studies, mercaptopurine tablets can impair female and male fertility [see Nonclinical Toxicology (13.1)]. The long-term effects of mercaptopurine on female and male fertility, including the reversibility have not been studied.

8.4 Pediatric Use

Safety and effectiveness of mercaptopurine tablets has been established in pediatric patients. Use of mercaptopurine tablets in pediatrics is supported by evidence from the published literature and clinical experience. Symptomatic hypoglycemia has been reported in pediatric patients with ALL receiving mercaptopurine. Reported cases were in pediatrics less than 6 years of age or with a low body mass index.

8.5 Geriatric Use

Clinical studies of mercaptopurine did not include sufficient numbers of subjects aged 65 and over to determine whether they respond differently from younger subjects. Other reported clinical experience has not identified differences in responses between the elderly and younger patients. In general, dose selection for an elderly patient should be cautious, usually starting at the low end of the dosing range, reflecting the greater frequency of decreased hepatic, renal, or cardiac function, and of concomitant disease or another drug therapy.

8.6 Renal Impairment

Use the lowest recommended starting dosage for mercaptopurine tablets or increase the dosing interval to every 36-48 hours in patients with renal impairment (CLcr less than 50 mL/min). Adjust the dose to maintain absolute neutrophil count (ANC) at a desirable level and for adverse reactions [see Dosage and Administration (2.3)].

8.7 Hepatic Impairment

Use the lowest recommended starting dosage for mercaptopurine tablets in patients with hepatic impairment. Adjust the dose to maintain absolute neutrophil count (ANC) at a desirable level and for adverse reactions [see Dosage and Administration (2.3)].

10 OVERDOSAGE

Signs and symptoms of mercaptopurine overdosage may be immediate (anorexia, nausea, vomiting, and diarrhea); or delayed (myelosuppression, liver dysfunction, and gastroenteritis). Dialysis cannot be expected to clear mercaptopurine. Hemodialysis is thought to be of marginal use due to the rapid intracellular incorporation of mercaptopurine into active metabolites with long persistence.
Withhold mercaptopurine tablets immediately for severe or life-threatening adverse reactions occur during treatment. If a patient is seen immediately following an accidental overdosage, it may be useful to induce emesis.

11 DESCRIPTION

Mercaptopurine is a nucleoside metabolic inhibitor, the chemical name is 6H-purine-6-thione, 1,7-dihydro-, monohydrate. The molecular formula is C5H4N4S • H2O and the molecular weight is 170.20. Its structural formula is:

Mercaptopurine is a yellow, crystalline powder. Mercaptopurine is practically insoluble in water and in ether. It has a pKa of 7.8, an average tapped density of 1.0 g/mL and average bulk density of 0.85 g/mL. It dissolves in solutions of alkali hydroxides.
Mercaptopurine tablets is available for oral use. Each scored tablet contains 50 mg mercaptopurine and the following inactive ingredients: corn starch, pregelatinized, potato starch, lactose, magnesium stearate and stearic acid.

12 CLINICAL PHARMACOLOGY

12.1 Mechanism of Action

Mercaptopurine is a purine analog that undergoes intracellular transport and activation to form metabolites including thioguanine nucleotides (TGNs). Incorporation of TGNs into DNA or RNA results in cell-cycle arrest and cell death. TGNs and other mercaptopurine metabolites are also inhibitors of de novo purine synthesis and purine nucleotide interconversions. Mercaptopurine was cytotoxic to proliferating cancer cells in vitro and had antitumor activity in mouse tumor models. It is not known which of the biochemical effects of mercaptopurine and its metabolites are directly or predominantly responsible for cell death.

12.2 Pharmacodynamics

Exposure-Response Relationships

Mercaptopurine exposure-response relationships and the time course of pharmacodynamics response are unknown.

12.3 Pharmacokinetics

Following a single oral dose of mercaptopurine 50 mg under fasted conditions to adult healthy subjects, the mean AUC0-INF was 129 h·ng/mL and Cmax was 69 ng/mL.
Absorption
Food Effect
Food has been shown to decrease the exposure of mercaptopurine.

Distribution
The volume of distribution usually exceeded that of the total body water. There is negligible entry of mercaptopurine into cerebrospinal fluid.

Plasma protein binding averages 19% over the concentration range 10 to 50 mcg/mL (a concentration only achieved by intravenous administration of mercaptopurine at doses exceeding 5 to 10 mg/kg).

Elimination
The elimination half-life is less than 2 hours following a single oral dose.

Metabolism
Mercaptopurine is inactivated via two major pathways. One is thiol methylation, which is catalyzed by the polymorphic enzyme thiopurine S-methyltransferase (TPMT), to form the inactive metabolite methyl-mercaptopurine. The second inactivation pathway is oxidation, which is catalyzed by xanthine oxidase. The product of oxidation is the inactive metabolite 6-thiouric acid.

Excretion
Following the oral administration of radiolabeled mercaptopurine, 46% of the dose was recovered in the urine (as parent drug and metabolites) in the first 24 hours.

12.5 Pharmacogenomics

Several published studies indicate that patients with reduced TPMT or NUDT15 activity receiving usual doses of mercaptopurine, accumulate excessive cellular concentrations of active 6-TGNs, and are at higher risk for severe myelosuppression. In a study of 1028 children with ALL, the approximate tolerated mercaptopurine dosage for patients with TPMT and/or NUDT15 deficiency on mercaptopurine maintenance therapy (as a percentage of the planned dosage) was as follows: heterozygous for either TPMT or NUDT15, 50-90%; heterozygous for both TPMT and NUDT15, 30-50%; homozygous for either TPMT or NUDT15, 5-10%.

Approximately 0.3% (1:300) of patients of European or African ancestry have two loss-of-function alleles of the TPMT gene and have little or no TPMT activity (homozygous deficient or poor metabolizers), and approximately 10% of patients have one loss-of-function TPMT allele leading to intermediate TPMT activity (heterozygous deficient or intermediate metabolizers). The TPMT*2, TPMT*3A, and TPMT*3C alleles account for about 95% of individuals with reduced levels of TPMT activity.

NUDT15 deficiency is detected in <1% of patients of European or African ancestry. Among patients of East Asian ancestry (i.e., Chinese, Japanese, Vietnamese), 2% have two loss-of-function alleles of the NUDT15 gene, and approximately 21% have one loss-of-function allele. The p.R139C variant of NUDT15 (present on the *2 and *3 alleles) is the most commonly observed, but other less common loss-of-function NUDT15 alleles have been observed.

Consider all clinical information when interpreting results from phenotypic testing used to determine the level of thiopurine nucleotides or TPMT activity in erythrocytes, since some coadministered drugs can influence measurement of TPMT activity in blood and blood from recent transfusions will misrepresent a patient’s actual TPMT activity [see Dosage and Administration (2.2), Warnings and Precautions (5.1)].

13 NONCLINICAL TOXICOLOGY

13.1 Carcinogenesis & Mutagenesis & Impairment Of Fertility

Mercaptopurine is carcinogenic in animals.
Mercaptopurine causes chromosomal aberrations in cells derived from animals and humans and induces dominant-lethal mutations in the germ cells of male mice.
Mercaptopurine can impair fertility. In mice, surviving female offspring of mothers who received chronic low doses of mercaptopurine during pregnancy were found sterile, or if they became pregnant, had smaller litters and more dead fetuses as compared to control animals.

15 REFERENCES

1. OSHA Hazardous Drugs. OSHA. http://www.osha.gov/SLTC/hazardousdrugs/index.html

16 HOW SUPPLIED/STORAGE AND HANDLING

Mercaptopurine tablets are supplied as biconvex, round, pale yellow to buff, scored tablets containing 50 mg mercaptopurine, imprinted with “9|3” available in:

- bottles of 25 NDC 71921-150-02
- bottles of 250 NDC 71921-150-25

Store at 20°C to 25°C (68°F to 77°F); excursions permitted to 15°C to 30°C (59°F to 86°F) [see USP Controlled Room Temperature]. Store in a dry place. Dispense in tight container as defined in the USP.

Mercaptopurine tablets is a cytotoxic drug. Follow special handling and disposal procedures.

17 PATIENT COUNSELING INFORMATION

Major Adverse Reactions
Advise patients and caregivers that mercaptopurine tablets can cause myelosuppression, hepatotoxicity, and gastrointestinal toxicity. Advise patients to contact their healthcare provider if they experience fever, sore throat, jaundice, nausea, vomiting, signs of local infection, bleeding from any site, or symptoms suggestive of anemia [see Warnings and Precautions (5.1, 5.2, 5.3)].

Embryo-Fetal Toxicity

- Advise pregnant women of the potential risk to a fetus. Advise females of reproductive potential to inform their healthcare provider of a known or suspected pregnancy [see Warnings and Precautions (5.2, 5.6), Use in Specific Populations (8.1)].
- Advise females of reproductive potential to use effective contraception during treatment with mercaptopurine tablets and for 6 months after the last dose [see Use in Specific Populations (8.3)].
- Advise males with female partners of reproductive potential to use effective contraception during treatment with mercaptopurine tablets and for 3 months after the last dose [see Use in Specific Populations (8.3), Nonclinical Toxicology (13.1)].

Lactation
Advise women not to breastfeed during treatment with mercaptopurine tablets and for 1 week after the last dose [see Use in Specific Populations (8.2)].
Infertility
Advise males and females of reproductive potential that mercaptopurine tablets can impair fertility [see Use in Specific Populations (8.3)].
Other Adverse Reactions
Instruct patients to minimize sun exposure due to risk of photosensitivity [see Adverse Reactions (6.1)].

Manufactured By:

Pinnacle Life Science Pvt. Ltd.

Baddi, Solan, HP174101, India

Manufactured For:

Florida Pharmaceutical Products, LLC

Boca Raton, FL 33487

Toll-Free # 1-800-315-0985

PACKAGE LABEL.PRINCIPAL DISPLAY PANEL

Mercaptopurine tablets

Container Label 25 Tablets

NDC 71921-150-02

Mercaptopurine tablets
Container Label 250 Tablets
NDC 71921-150-25